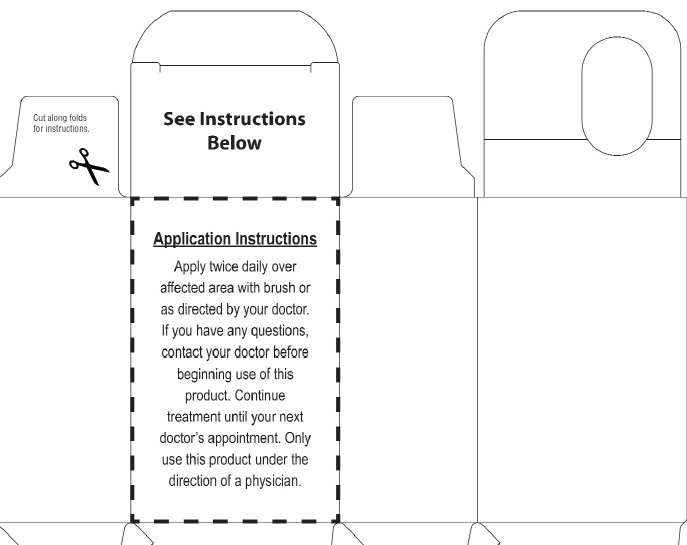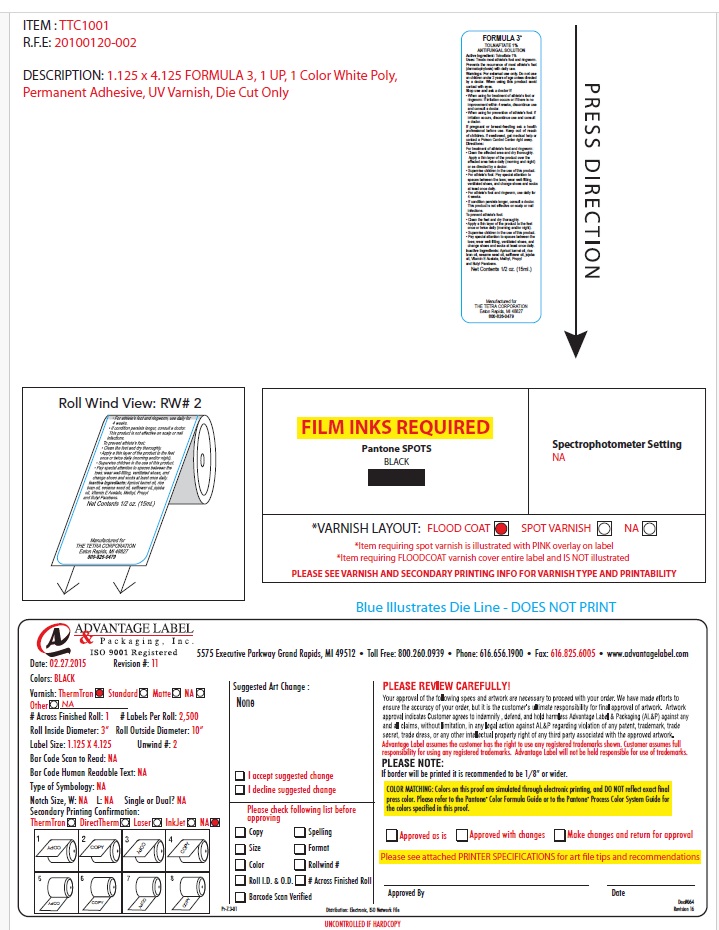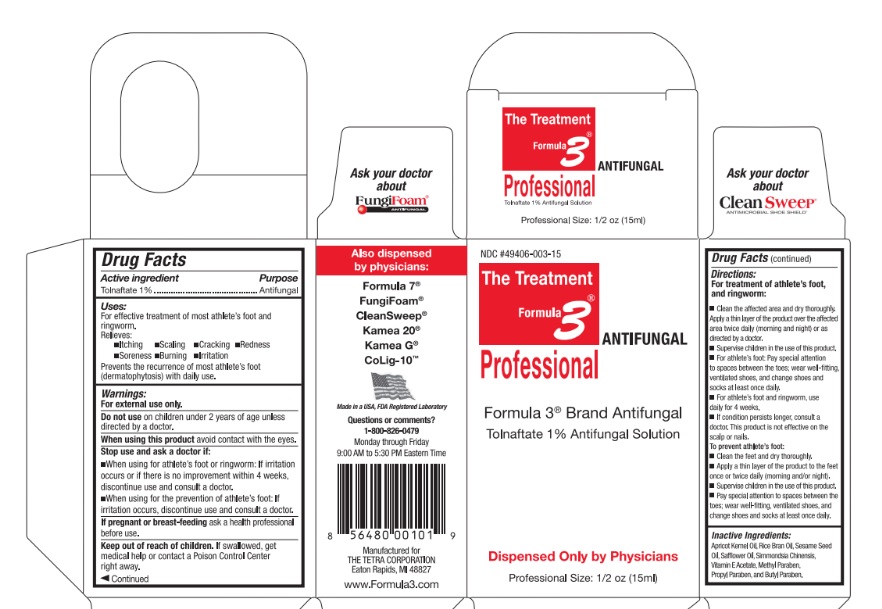 DRUG LABEL: Formula 3
NDC: 49406-003 | Form: SOLUTION
Manufacturer: The Tetra Corporation
Category: otc | Type: HUMAN OTC DRUG LABEL
Date: 20250818

ACTIVE INGREDIENTS: TOLNAFTATE 10 mg/1 mL
INACTIVE INGREDIENTS: APRICOT KERNEL OIL; RICE BRAN OIL; SESAME OIL; SAFFLOWER OIL; JOJOBA OIL; .ALPHA.-TOCOPHEROL ACETATE; METHYLPARABEN; PROPYLPARABEN; BUTYLPARABEN

Active ingredient:

Tolnaftate 1%

Purpose

Antifungal

Uses:

For effective treatment of most athlete's foot and ringworm.

Relieves:

- Itching
- Soreness
- Scaling
- Burning
- Cracking
- Irritation
- Redness

Prevents the recurrence of most athlete's foot (dermatophytosis) with daily use.

Warnings

For external use only.

Do not useon children under 2 years of age unless directed by a doctor.

When using this productavoid contact with eyes.

Stop use and ask a doctor if

- When using for athlete's foot or ringworm: If irritation occurs or if there is no improvement within 4 weeks, discontinue use and consult a doctor.
- When using for the prevention of athlete's foot: If irritation occurs,discontinue use and consult a doctor.

If pregnant or breastfeedingask a health professional before use.

Keep out of reach of children.

If swallowed, get medical help or contact a Poison Control Center right away.

Directions

For treatment of athlete's foot and ringworm

- Clean the affected area and dry thoroughly. Apply a thin layer of the product over affected area twice daily (morning and night) or as directed by a doctor.
- Supervise children in the use of this product.
- For athlete's foot: Pay special attention to spaces between the toes; wear well fitting, ventilated shoes, and change shoes and socks at least once daily.
- For athlete's foot and ringworm, use daily for 4 weeks.
- If condition persists longer, consult a doctor. This product is not effective on scalp or nail.

To prevent athlete's foot:

- Clean the feet and dry thoroughly.
- Apply a thin layer of the product to the feet once or twice daily (morning and/or night)
- Supervise children in the use of this product.
- Pay special attention to spaces between the toes; wear well fitting, ventilated shoes, and change shoes and socks at least once daily.

Inactive ingredients

Apricot Kernel Oil, Rice Bran Oil, Sesame Seed Oil, Safflower Oil, simmondsia chinensis, Vitamin E Acetate, Methyl Paraben, Propyl Paraben and Butyl Paraben.